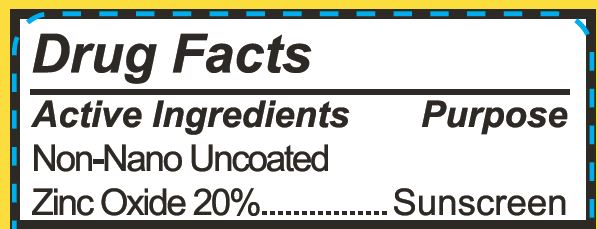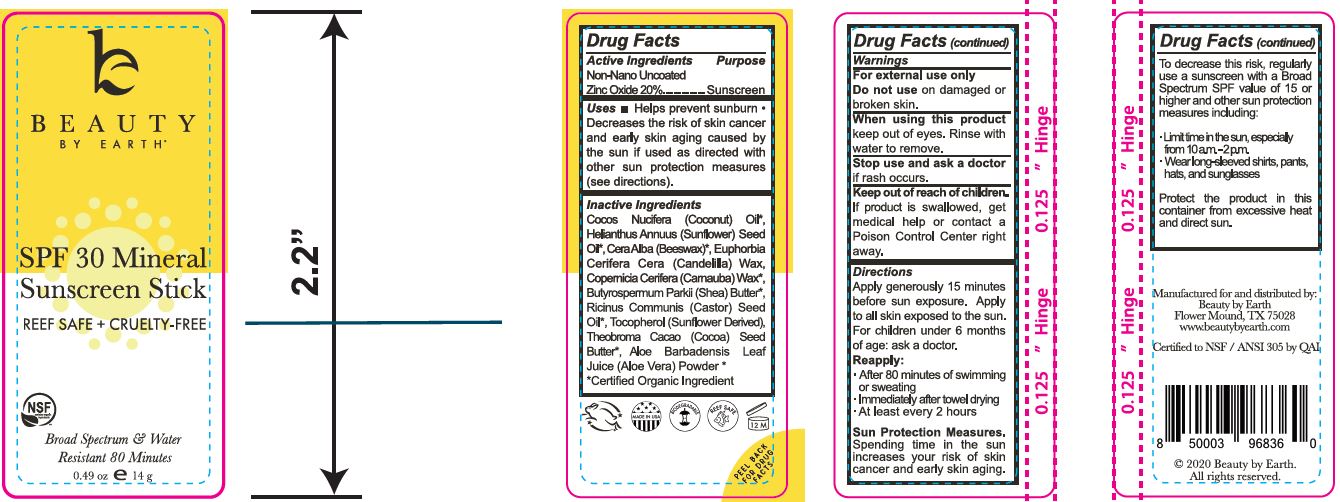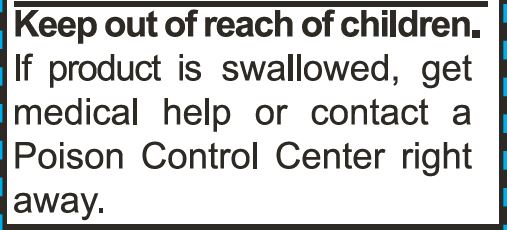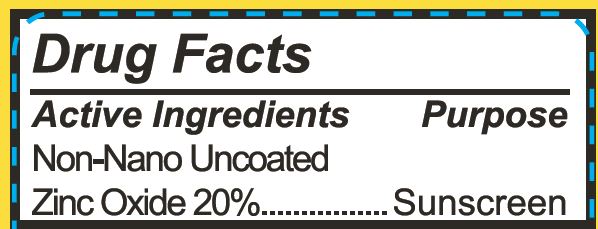 DRUG LABEL: Facial Sunscreen Stick, SPF 30
NDC: 62932-223 | Form: STICK
Manufacturer: Private Label Select Ltd CO
Category: otc | Type: HUMAN OTC DRUG LABEL
Date: 20201228

ACTIVE INGREDIENTS: ZINC OXIDE 20 g/100 g
INACTIVE INGREDIENTS: CARNAUBA WAX; SUNFLOWER OIL; CANDELILLA WAX; .ALPHA.-TOCOPHEROL, D-; .GAMMA.-TOCOPHEROL; .DELTA.-TOCOPHEROL; COCONUT OIL; WHITE WAX; SHEA BUTTER; CASTOR OIL; COCOA BUTTER; .BETA.-TOCOPHEROL; ALOE VERA LEAF

Beauty By Earth Facial Sunscreen Stick, SPF 30